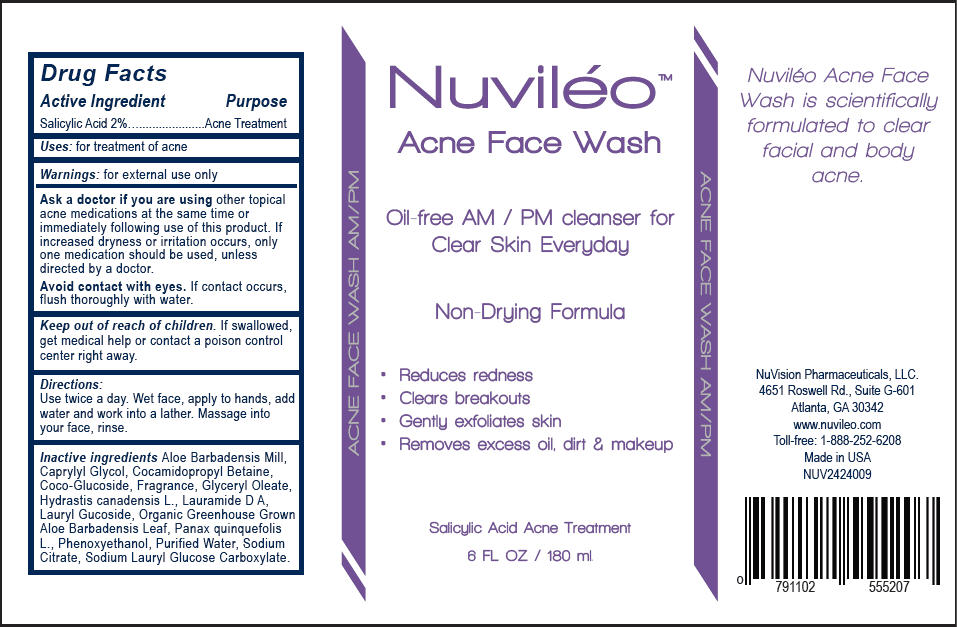 DRUG LABEL: Nuvileo Acne Face Wash
NDC: 58133-501 | Form: SOLUTION, GEL FORMING / DROPS
Manufacturer: Cosmetic Specialty Labs, Inc.
Category: otc | Type: HUMAN OTC DRUG LABEL
Date: 20150715

ACTIVE INGREDIENTS: Salicylic Acid 20 mg/1 mL
INACTIVE INGREDIENTS: Aloe Vera Whole; Caprylyl Glycol; Cocamidopropyl Betaine; Coco Glucoside; Glyceryl Oleate; Hydrastis Canadensis Whole; Lauryl Glucoside; Panax Quinquefolius Whole; Phenoxyethanol; Water; Sodium Citrate

Nuviléo™ Acne Face Wash

Drug Facts

Active Ingredient

Salicylic Acid 2%

Purpose

Acne Treatment

Uses

for treatment of acne

Warnings

for external use only

Ask a doctor if you are using other topical acne medications at the same time or immediately following use of this product. If increased dryness or irritation occurs, only one medication should be used, unless directed by a doctor.

Avoid contact with eyes. If contact occurs, flush thoroughly with water.

Keep out of reach of children. If swallowed, get medical help or contact a poison control center right away.

Directions

Use twice a day. Wet face, apply to hands, add water and work into a lather. Massage into your face, rinse.

Inactive ingredients

Aloe Barbadensis Mill, Caprylyl Glycol, Cocamidopropyl Betaine, Coco-Glucoside, Fragrance, Glyceryl Oleate, Hydrastis canadensis L., Lauramide D A, Lauryl Gucoside, Organic Greenhouse Grown Aloe Barbadensis Leaf, Panax quinquefolis L., Phenoxyethanol, Purified Water, Sodium Citrate, Sodium Lauryl Glucose Carboxylate.

PRINCIPAL DISPLAY PANEL - 180 ml Bottle Label

Nuviléo™
Acne Face Wash

Oil-free AM / PM cleanser for
Clear Skin Everyday

Non-Drying Formula

- Reduces redness
- Clears breakouts
- Gently exfoliates skin
- Removes excess oil, dirt & makeup

Salicylic Acid Acne Treatment

6 FL. OZ. / 180 ml.